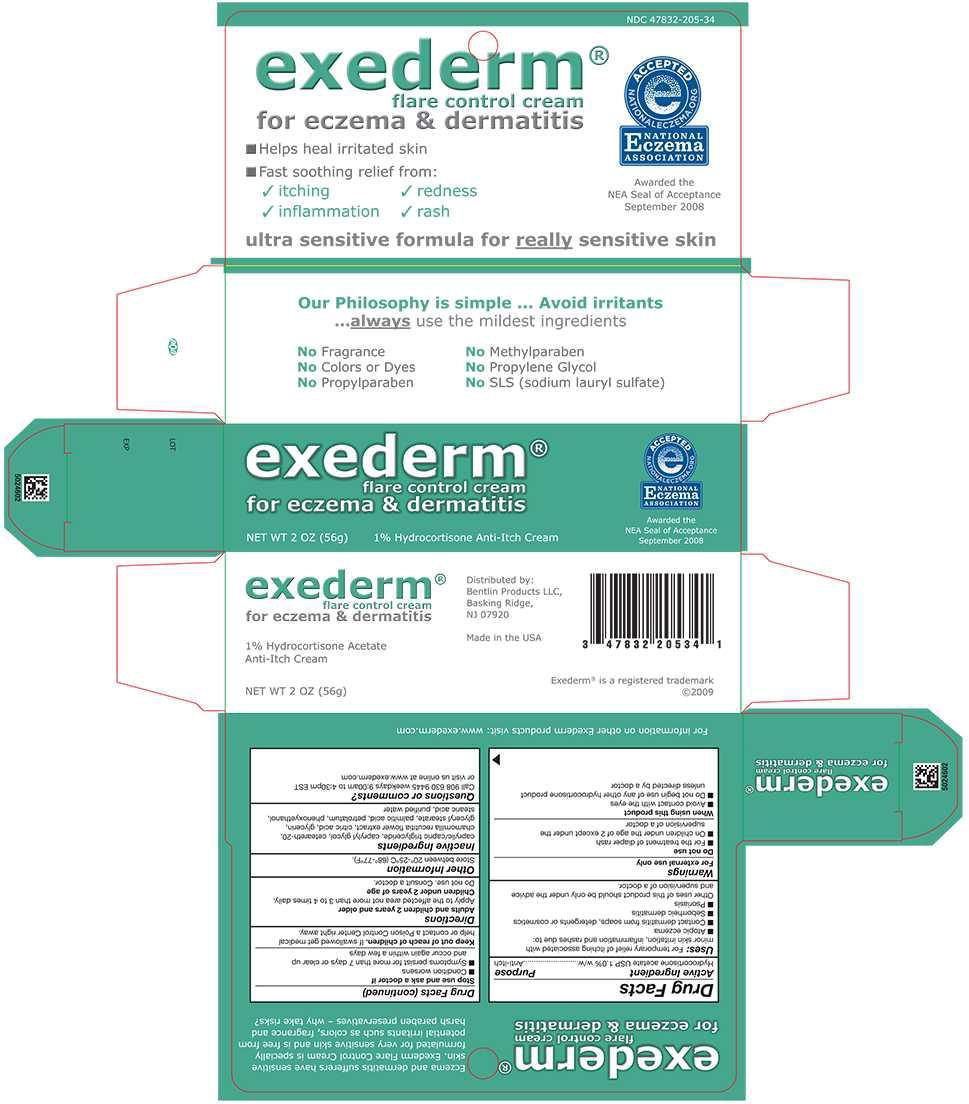 DRUG LABEL: Hydrocortisone Acetate
NDC: 47832-205 | Form: CREAM
Manufacturer: Bentlin Products LLC
Category: otc | Type: HUMAN OTC DRUG LABEL
Date: 20231030

ACTIVE INGREDIENTS: HYDROCORTISONE ACETATE 10 mg/1 g
INACTIVE INGREDIENTS: GLYCERIN; WATER; PETROLATUM; MEDIUM-CHAIN TRIGLYCERIDES; GLYCERYL STEARATE SE; PALMITIC ACID; POLYOXYL 20 CETOSTEARYL ETHER; CHAMOMILE; ANHYDROUS CITRIC ACID; PHENOXYETHANOL

Drug Facts

Active Ingredient

Hydrocortisone acetate USP 1.0% w/w

Purpose

Anti-itch

Uses:

For temporary relief of itching associated with minor skin irritation, inflammation and rashes due to:

- Atopic eczema
- Contact dermatitis from soaps, detergents or cosmetics
- Seborrheic dermatitis
- Psoriasis

Other uses of this product should be only under the advice and supervision of a doctor

Warnings

For external use only

Do not use

- For the treatment of diaper rash
- On children under the age of 2 except under the supervision of a doctor

When using this product

- Avoid contact with the eyes
- Do not begin use any other hydrocortisone product unless directed by a doctor

Stop use and ask a doctor if

- Condition worsens
- Symptoms persist for more than 7 days or clear up and occur again within a few days

Keep out of reach of children. If swallowed get medical help or contact a Poison Control Center right away.

Directions

Adults and children 2 years and older

Apply to the affected area not more than 3 to 4 times daily.

Children under 2 years of age

Do not use. Consult a doctor.

Other Information

Store between 20°-25°C (68°-77°F)

Inactive Ingredients

caprylic/capric triglyceride, caprytyl glycol, ceteareth-20, chamomillia recutitia flower extract, citric acid, glycerin, glyceryl, stearate, palmitic acid. petrolatum phenoxyethanol, stearic acid, purified water

Questions or comments?

Call 908 630 9445 weekdays 9:00am to 4:30pm EST or visit us online at www.exederm.com

Principal Display Panel - 2 oz Carton Label

NDC 47832-205-34

exederm®

flare control cream
for eczema & dermatitis

NET WT 2 OZ (56g)

1% Hydrocortisone Anti-Itch Cream